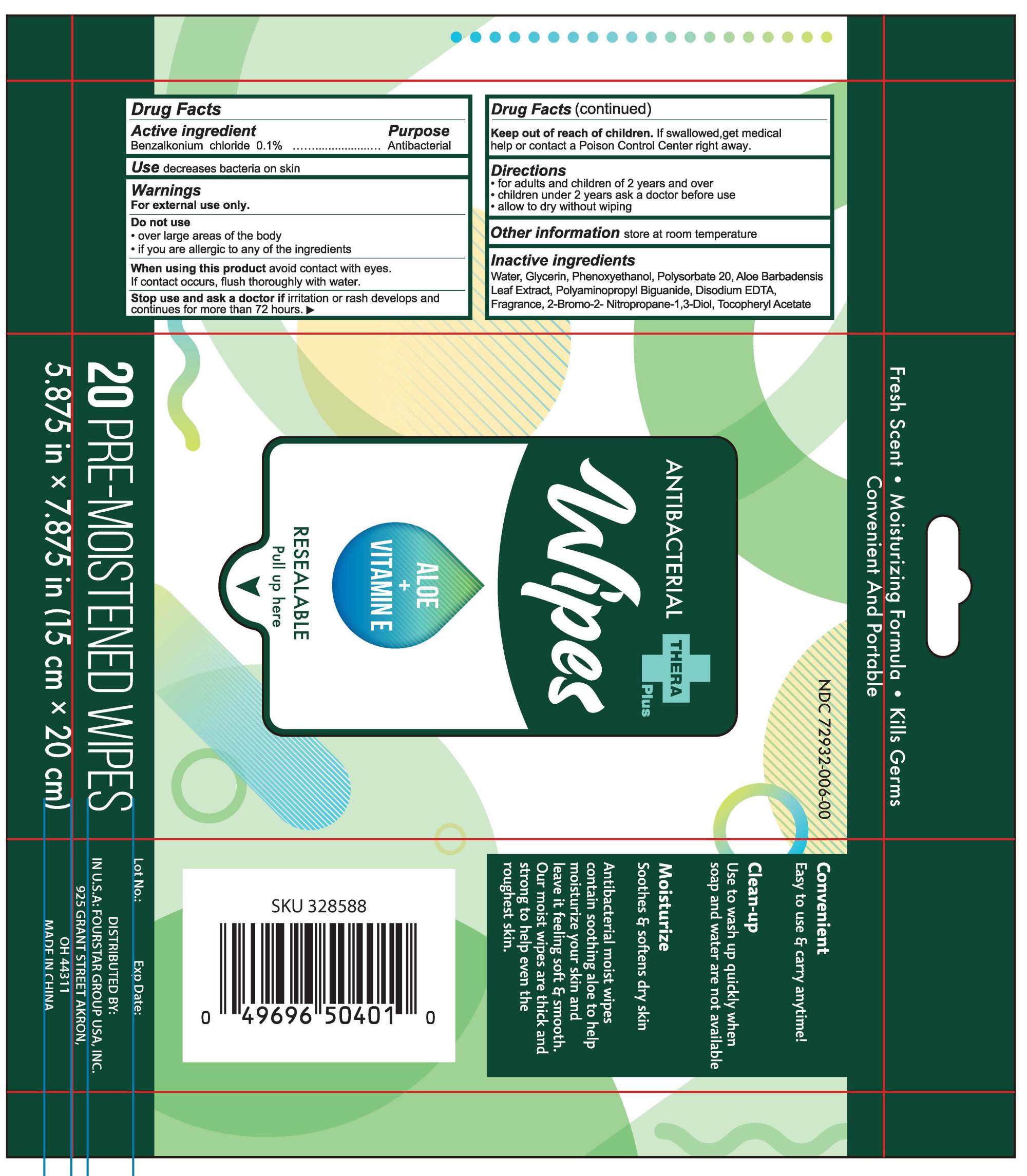 DRUG LABEL: Antibacterial Wipes
NDC: 59575-800 | Form: CLOTH
Manufacturer: Hebei Yihoucheng Commodity Co.,Ltd.
Category: otc | Type: HUMAN OTC DRUG LABEL
Date: 20201230

ACTIVE INGREDIENTS: BENZALKONIUM CHLORIDE 0.1 g/100 g
INACTIVE INGREDIENTS: ALPHA-TOCOPHEROL ACETATE; ALOE VERA LEAF; PHENOXYETHANOL; GLYCERIN; POLYSORBATE 20; POLYAMINOPROPYL BIGUANIDE; DISODIUM EDTA-COPPER; BRONOPOL; WATER

59575-800 ANTIBACTERIAL WIPES 0.1%Benzalkonium chloride

Active ingredient

Benzalkonium chloride 0.1%

Purpose

Antibacterial

Use

decreases bacteria on skin

Warnings

For external use only.
Do not use
over large areas of the body
if you are allergic to any of the ingredients
When using this product avoid contact with eyes.
lf contact occurs, flush thoroughly with water.
Stop use and ask a doctor if irritation or rash develops and
continues for more than 72 hours.

Keep out of reach of children

if swallowed
get medical help or contact a Poison Control Center right away.

Directions

for adults and children of 2 years and over
children under 2 years ask a doctor before use allow to dry without wiping

INACTIVE INGREDIENT

Water, Glycerin, Phenoxyethanol, Polysorbate 20,Aloe Barbadensis
Leaf Extract， Polyaminopropyl Biguanide, Disodium EDTA,
Fragrance, 2-Bromo-2-Nitropropane-1,3-Diol,Tocopheryl Acetate